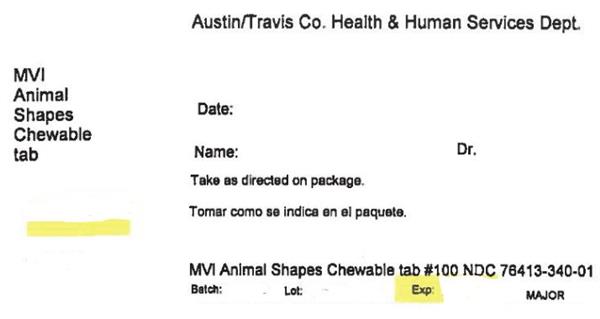 DRUG LABEL: Animal Shapes
NDC: 76413-340 | Form: TABLET, CHEWABLE
Manufacturer: Central Texas Community Health Centers
Category: other | Type: DIETARY SUPPLEMENT
Date: 20190109

ACTIVE INGREDIENTS: VITAMIN A 2500 [iU]/1 1; ASCORBIC ACID 60 mg/1 1; CHOLECALCIFEROL 400 [iU]/1 1; .ALPHA.-TOCOPHEROL 15 [iU]/1 1; THIAMINE 1.05 mg/1 1; RIBOFLAVIN 1.2 mg/1 1; NIACIN 13.5 mg/1 1; PYRIDOXINE 1.05 mg/1 1; FOLIC ACID 0.3 mg/1 1; CYANOCOBALAMIN 4.5 ug/1 1
INACTIVE INGREDIENTS: Sorbitol; Sucrose; Gelatin, Unspecified; stearic acid; Citric Acid Monohydrate; Silicon Dioxide; Starch, Corn; magnesium stearate; microcrystalline cellulose; FD&C Red NO. 40; Aluminum Oxide; Sucralose; FD&C Yellow NO. 6; Anhydrous Dibasic Calcium Phosphate; sodium ascorbate; FD&C Blue NO. 2; Sodium Benzoate; Tocopherol; Sorbic acid; Butylated Hydroxytoluene

Animal SHAPES

STATEMENT OF IDENTITY

Supplement Facts
Serving Size: 1 Tablet
Amount Per Serving |  | % DV [% Daily Value (DV) for Children 2-3 years of age.] | % DV [% Daily Value (DV) for Adults and Children 4 or more years of age.]
Vitamin A (as Acetate) | 2,500 I.U. | 100% | 50%
Vitamin C (as Ascorbic Acid and Sodium Ascorbate) | 60 mg. | 150% | 100%
Vitamin D-3 (as Cholecalciferol) | 400 I.U. | 100% | 100%
Vitamin E (as dl-Alpha Tocopheryl Acetate) | 15 I.U. | 150% | 50%
Vitamin B-1 (as Thiamine Mononitrate) | 1.05 mg. | 150% | 70%
Vitamin B-2 (Riboflavin) | 1.2 mg. | 150% | 70%
Niacin (as Niacinamide) | 13.5 mg. | 150% | 67%
Vitamin B-6 (as Pyridoxine HCl) | 1.05 mg. | 150% | 52%
Folic Acid | 0.3 mg. | 150% | 75%
Vitamin B-12 (as Cyanocobalamin) | 4.5 mcg. | 150% | 75%

OTHER INGREDIENTS: Sorbitol, Sugar, Gelatin, Stearic Acid, Citric Acid, Silica, Unsaturated Mono & Diglycerides, Starch, Magnesium Stearate, Cherry Flavor, Orange Flavor, Grape Flavor, Microcrystalline Cellulose, FD&C Red #40 Lake, Sucralose, FD&C Yellow #6 Lake, Dicalcium Phosphate, Sodium Ascorbate, FD&C Blue #2 Lake, Triglycerides, Sodium Benzoate, Tocopherols, Sorbic Acid and BHT.

Cherry flavor contains: Modified Corn Starch Grape flavor contains: Maltodextrin, Modified Corn Starch and Silica Orange flavor contains: Maltodextrin, Lactose [Contains: Milk] , Natural Flavoring, Modified Corn Starch and Sugar

DIRECTIONS

For adults and children 2 years of age and older, chew one (1) tablet daily, preferably with a meal. As a reminder, discuss the supplements and medications you take with your health care providers.

WARNING

If you are pregnant, nursing, taking any medications or planning any medical procedure, consult your doctor before use. Discontinue use and consult your doctor if any adverse reactions occur. THIS PRODUCT IS INTENDED FOR USE BY CHILDREN UNDER ADULT SUPERVISION.

SAFE HANDLING WARNING

KEEP OUT OF THE REACH OF CHILDREN. STORE AT ROOM TEMPERATURE AND AVOID EXCESSIVE HEAT. TAMPER RESISTANT: DO NOT USE IF SEAL UNDER CAP IS BROKEN OR MISSING.

HEALTH CLAIM

Distributed by: MAJOR® PHARMACEUTICALS
31778 Enterprise Drive, Livonia, MI 48150, USA
Questions or Comments? (800) 616-2471

M-29
11382-06-16
Rev. 06/16